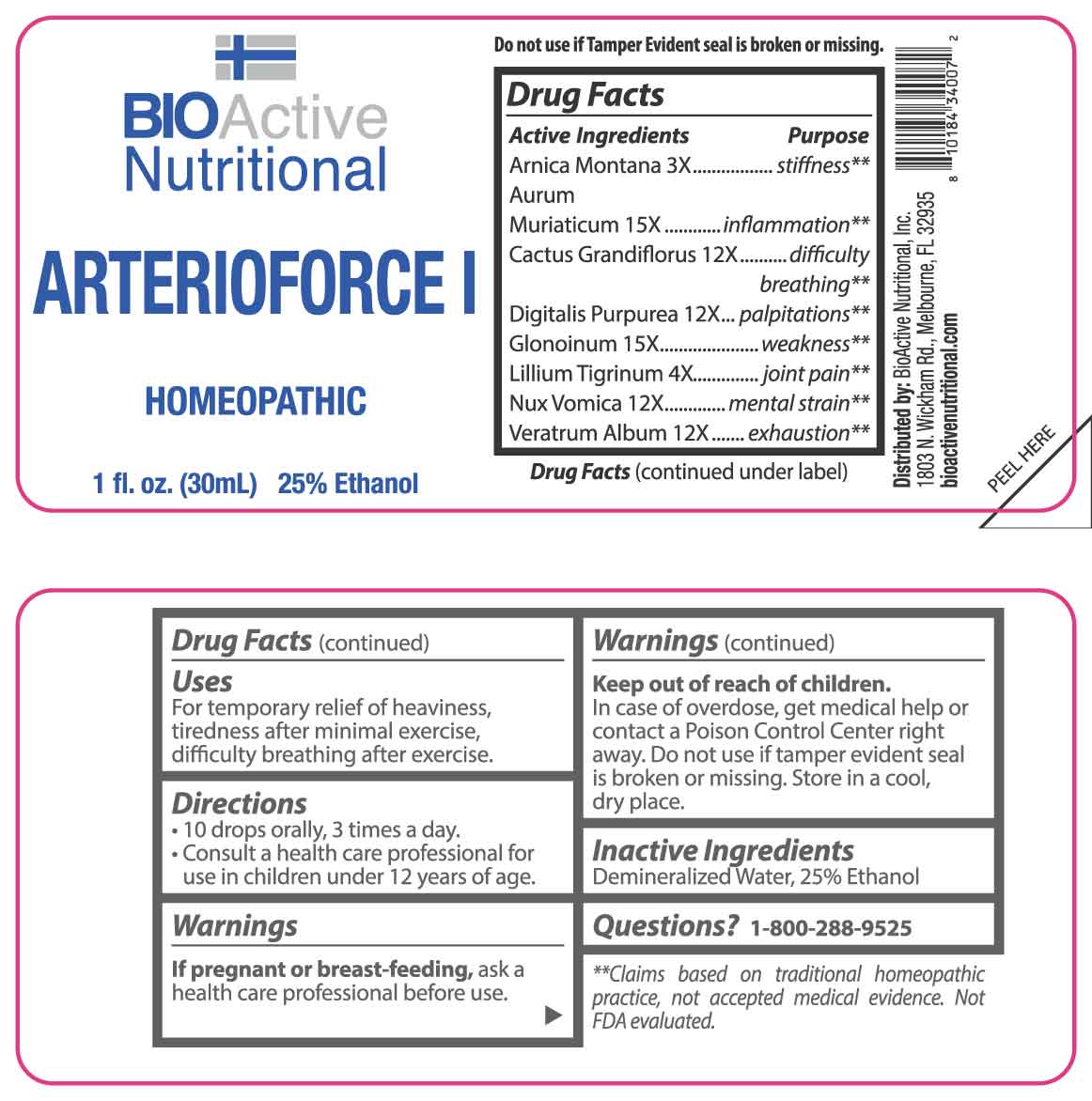 DRUG LABEL: Arterioforce I
NDC: 43857-0656 | Form: LIQUID
Manufacturer: BioActive Nutritional, Inc.
Category: homeopathic | Type: HUMAN OTC DRUG LABEL
Date: 20250416

ACTIVE INGREDIENTS: ARNICA MONTANA WHOLE 3 [hp_X]/1 mL; LILIUM LANCIFOLIUM WHOLE FLOWERING 4 [hp_X]/1 mL; GOLD TRICHLORIDE 15 [hp_X]/1 mL; SELENICEREUS GRANDIFLORUS STEM 12 [hp_X]/1 mL; DIGITALIS 12 [hp_X]/1 mL; NITROGLYCERIN 15 [hp_X]/1 mL; STRYCHNOS NUX-VOMICA SEED 12 [hp_X]/1 mL; VERATRUM ALBUM ROOT 12 [hp_X]/1 mL
INACTIVE INGREDIENTS: WATER; ALCOHOL

DRUG FACTS:

ACTIVE INGREDIENTS:

Arnica Montana 3X, Aurum Muriaticum 15X, Cactus Grandiflorus 12X, Digitalis Purpurea 12X, Glonoinum 15X, Lilium Tigrinum 4X, Nux Vomica 12X, Veratrum Album 12X.

PURPOSE:

Arnica Montana – stiffness,** Aurum Muriaticum - inflammation,** Cactus Grandiflorus – difficulty breathing,** Digitalis Purpurea - palpitations,** Glonoinum - weakness,** Lilium Tigrinum – joint pain,** Nux Vomica – mental strain,** Veratrum Album – exhaustion**

**Claims based on traditional homeopathic practice, not accepted medical evidence. Not FDA evaluated.

USES:

For temporary relief of heaviness, tiredness after minimal exercise, difficulty breathing after exercise.

WARNINGS:

If pregnant or breast-feeding, ask a health care professional before use.

Keep out of reach of children. In case of overdose, get medical help or contact a Poison Control Center right away.

Do not use if tamper evident seal is broken or missing.

Store in a cool, dry place.

KEEP OUT OF REACH OF CHILDREN:

In case of overdose, get medical help or contact a Poison Control Center right away.

DIRECTIONS:

• 10 drops orally, 3 times a day.

Consult a physician for use in children under 12 years of age.

INACTIVE INGREDIENTS:

Demineralized Water, 25% Ethanol

QUESTIONS:

Distributed by:

BioActive Nutritional, Inc.

1803 N. Wickham Rd.

Melbourne, FL 32935

bioactivenutritional.com

1-800-288-9525

PACKAGE LABEL DISPLAY:

BIOActive Nutritional

ARTERIOFORCE I

HOMEOPATHIC

1 FL OZ (30 ml)